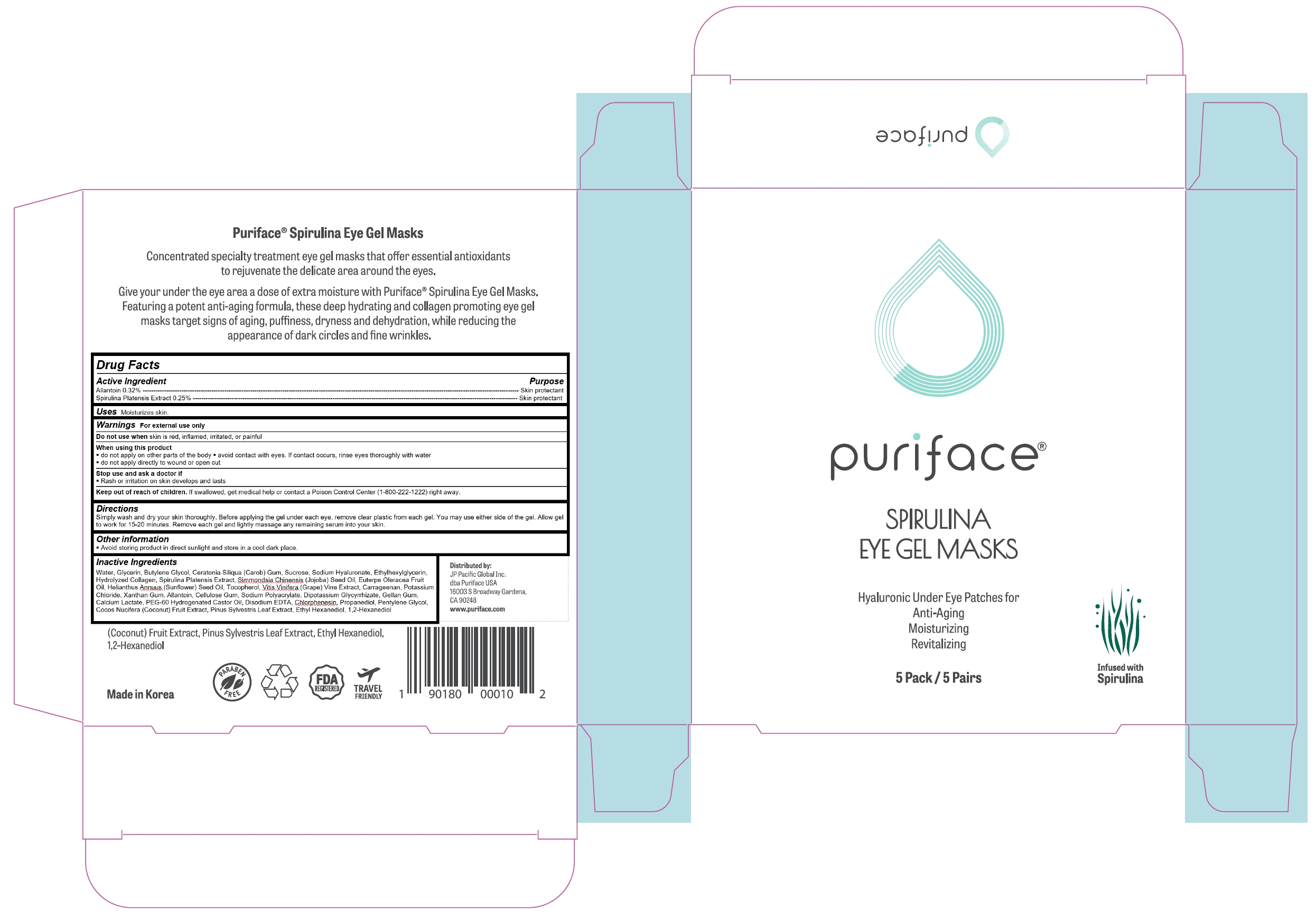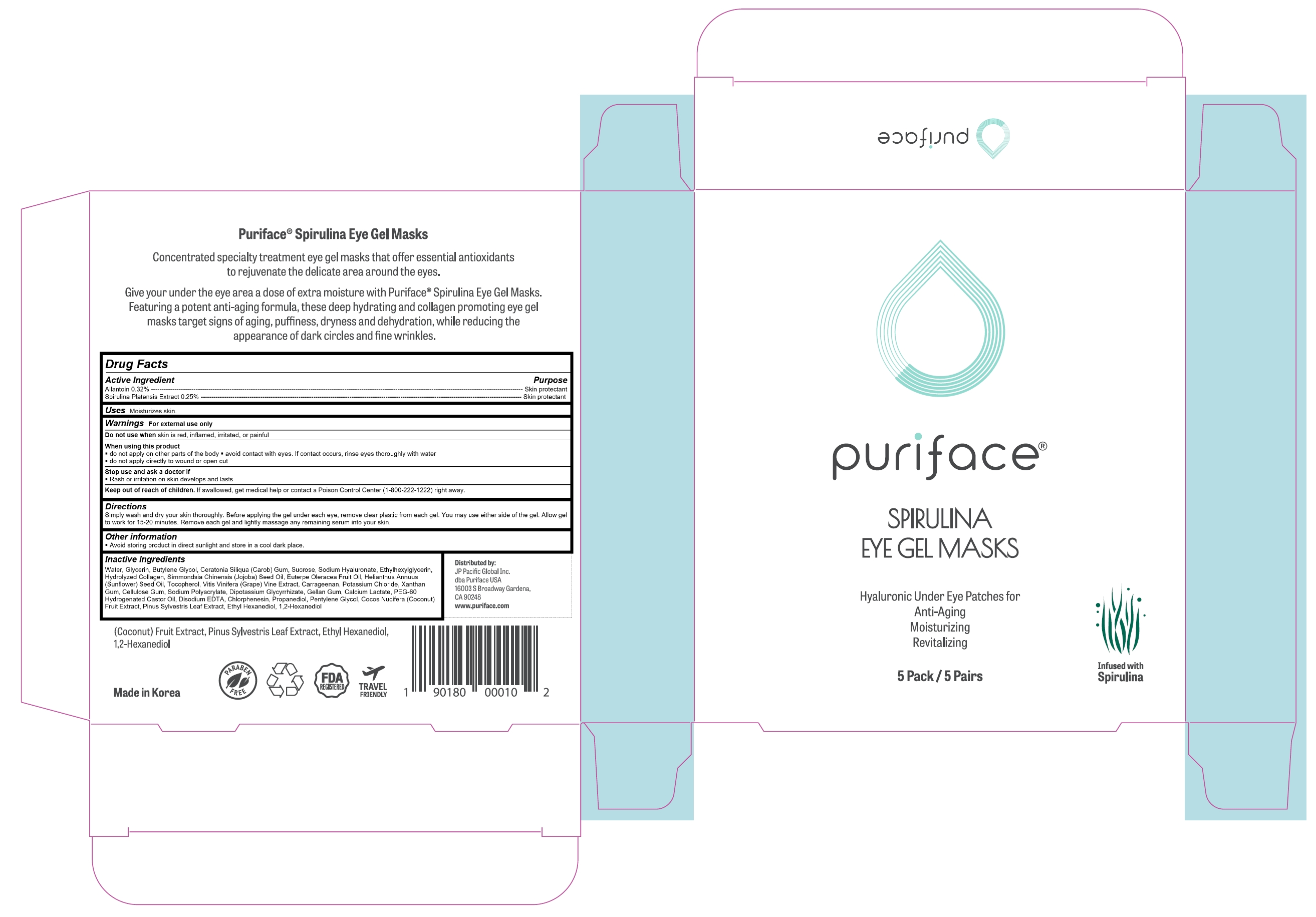 DRUG LABEL: Puriface Spirulina Eye Gel Masks
NDC: 71727-104 | Form: PATCH
Manufacturer: iMode Korea, Inc.
Category: otc | Type: HUMAN OTC DRUG LABEL
Date: 20190208

ACTIVE INGREDIENTS: ALLANTOIN 0.0864 g/27 mL; SPIRULINA PLATENSIS 0.0675 g/27 mL
INACTIVE INGREDIENTS: WATER

Puriface Spirulina Eye Gel Masks

Active ingredients

Allantoin

Spirulina Platensis Extract

Purpose

Skin protectant

Uses

Moisturizes skin.

Warnings

For external use only

Do not use when skin is red, inflamed, irritated, or painful

When using this product

- do not apply on other parts of the body avoid contact with eyes. If contact occurs, rinse eyes thoroughly with water

- do not apply directly to wound or open cut

Stop use and ask a doctor if

- Rash or irritation on skin develops and lasts

Keep out of reach of children

If swallowed, get medical help or contact a Poison Control Center (1-800-222-1222) right away.

Directions

Simply wash and dry your skin thoroughly. Before applying the gel under each eye, remove clear plastic from each gel. You may use either side of the gel. Allow gel to work for 15-20 minutes. Remove each gel and lightly massage any remaining serum into your skin.

Inactive ingredients

Water, Glycerin, Butylene Glycol, Ceratonia Siliqua (Carob) Gum, Sucrose, Sodium Hyaluronate, Ethylhexylglycerin, Hydrolyzed Collagen, Simmondsia Chinensis (Jojoba) Seed Oil, Euterpe Oleracea Fruit Oil, Helianthus Annuus (Sunflower) Seed Oil, Tocopherol, Vitis Vinifera (Grape) Vine Extract, Carrageenan, Potassium Chloride, Xanthan Gum, Cellulose Gum, Sodium Polyacrylate, Dipotassium Glycyrrhizate, Gellan Gum, Calcium Lactate, PEG-60 Hydrogenated Castor Oil, Disodium EDTA, Chlorphenesin, Propanediol, Pentylene Glycol, Cocos Nucifera (Coconut) Fruit Extract, Pinus Sylvestris Leaf Extract, Ethyl Hexanediol, 1,2-Hexanediol